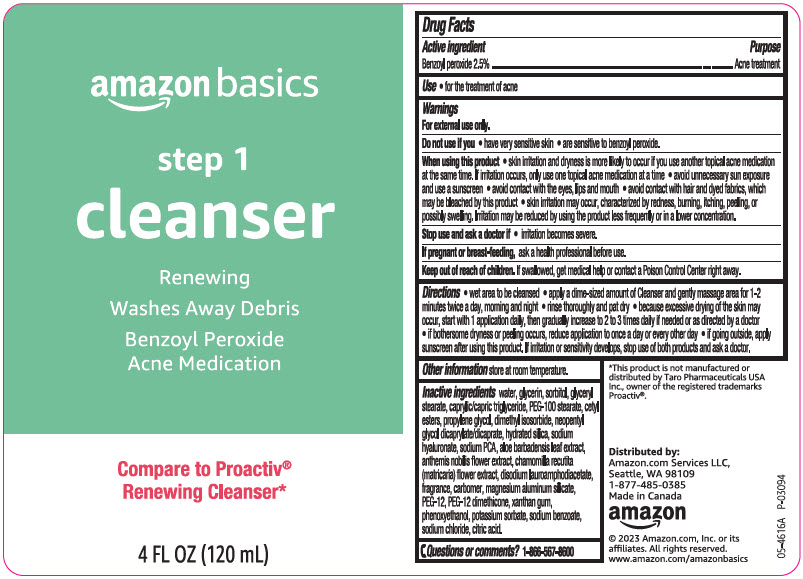 DRUG LABEL: amazon basics step 1 cleanser
NDC: 72288-120 | Form: LOTION
Manufacturer: AMAZON.COM SERVICES LLC
Category: otc | Type: HUMAN OTC DRUG LABEL
Date: 20240826

ACTIVE INGREDIENTS: BENZOYL PEROXIDE 25 mg/1 mL
INACTIVE INGREDIENTS: Water; Glycerin; Sorbitol; GLYCERYL MONOSTEARATE; MEDIUM-CHAIN TRIGLYCERIDES; PEG-100 Stearate; CETYL ESTERS WAX; Propylene Glycol; Dimethyl Isosorbide; Neopentyl Glycol Dicaprylate/Dicaprate; Hydrated Silica; HYALURONATE SODIUM; SODIUM PYRROLIDONE CARBOXYLATE; ALOE VERA LEAF; CHAMAEMELUM NOBILE FLOWER; CHAMOMILE; Disodium Lauroamphodiacetate; CARBOMER HOMOPOLYMER, UNSPECIFIED TYPE; Magnesium Aluminum Silicate; POLYETHYLENE GLYCOL 600; PEG-12 DIMETHICONE (300 CST); Xanthan Gum; Phenoxyethanol; Potassium Sorbate; Sodium Benzoate; Sodium Chloride; CITRIC ACID MONOHYDRATE

amazon basics step 1 cleanser
Acne treatment

Drug Facts

Active ingredient

Benzoyl peroxide 2.5%

Purpose

Acne Treatment

Use

for the treatment of acne

Warnings

For external use only

Do not use if you

- have very sensitive skin
- are sensitive to benzoyl peroxide.

When using this product

- skin irritation and dryness is more likely to occur if you use another topical acne medication at the same time. If irritation occurs, only use one topical acne medication at a time.
- avoid unnecessary sun exposure and use a sunscreen
- avoid contact with the eyes, lips, and mouth
- avoid contact with hair and dyed fabrics, which may be bleached by this product
- skin irritation may occur, characterized by redness, burning, itching, peeling, or possibly swelling. Irritation may be reduced by using the product less frequently or in a lower concentration.

Stop use and ask a doctor if

- irritation becomes severe.

PREGNANCY OR BREAST FEEDING

If pregnant or breast-feeding, ask a health professional before use.

Keep out of reach of children. If swallowed, get medical help or contact a Poison Control Center right away.

Directions

- wet area to be cleansed
- apply a dime-sized amount of Cleanser and gently massage area for 1-2 minutes twice a day, morning and night
- rinse thoroughly and pat dry
- because excessive drying of the skin may occur, start with 1 application daily, then gradually increase to 2 to 3 times daily if needed or as directed by a doctor
- if bothersome dryness or peeling occurs, reduce application to once a day or every other day
- if going outside, apply sunscreen after using this product. If irritation or sensitivity develops, stop use of both products and ask a doctor.

Other information

store at room temperature.

Inactive ingredients

water, glycerin, sorbitol, glyceryl stearate, caprylic/capric triglyceride, PEG-100 stearate, cetyl esters, propylene glycol, dimethyl isosrbide, neopentyl glycol dicaprylate/dicaprate, hydrated silica, sodium hyaluronate, sodium PCA, aloe barbadensis leaf extract, anthemis nobilis flower extract, chamomilla recutita (matricaria) flower extract, disodium lauroamphodiacetate, fragrance, carbomer, magnesium aluminum silicate, PEG-12, PEG-12 dimethicone, xanthan gum, phenoxyethanol, potassium sorbate, sodium benzoate, sodium chloride, citric acid.

Questions or comments?

1-866-567-8600

Distributed by:
Amazon.com Services LLC,
Seattle, WA 98109

PRINCIPAL DISPLAY PANEL - 120 mL Bottle Label

amazon basics

step 1

cleanser

Renewing

Washes Away Debris

Benzoyl Peroxide
Acne Medication

Compare to Proactiv®
Renewing Cleanser*

4 FL OZ (120 mL)